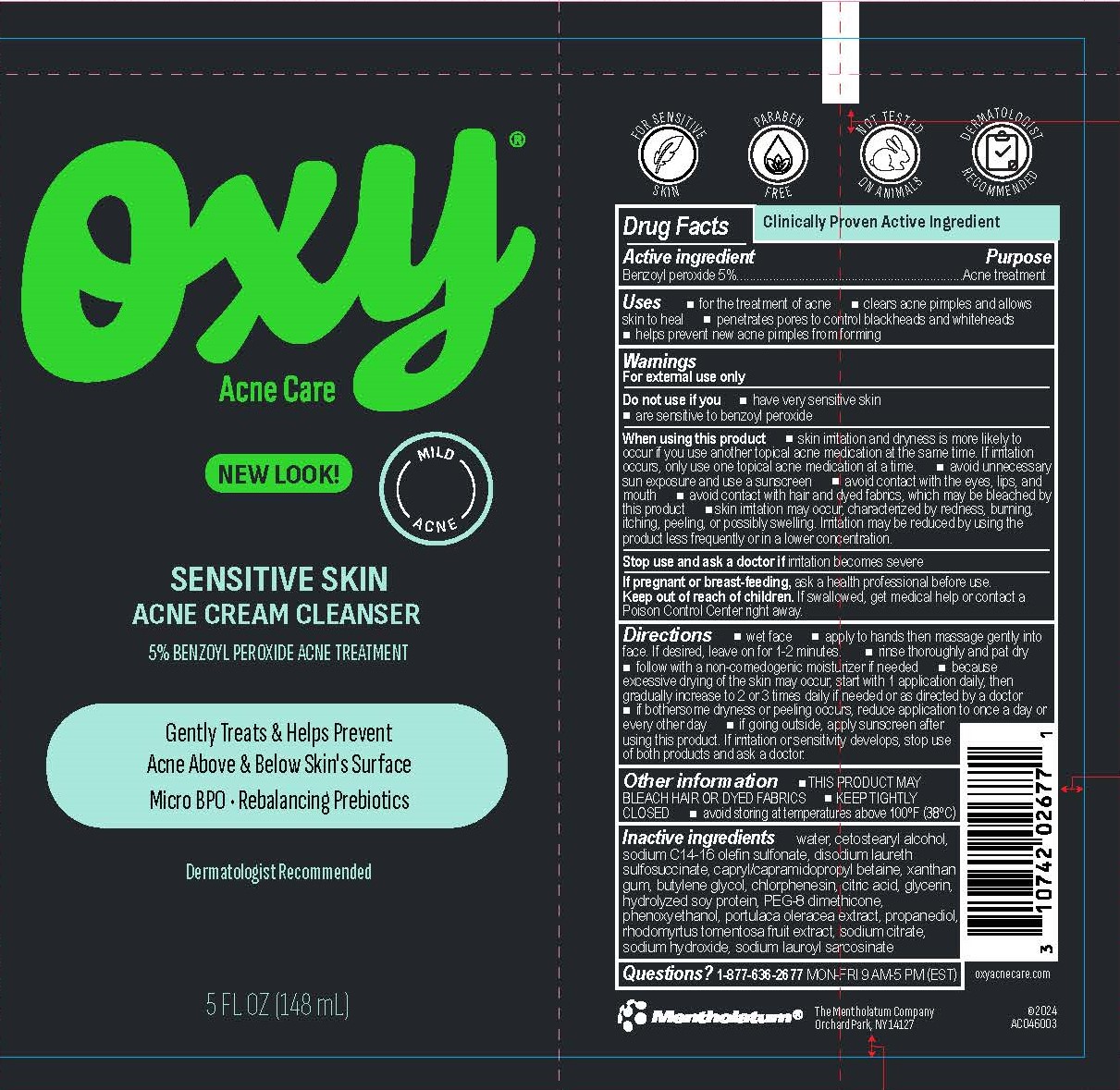 DRUG LABEL: Oxy Sensitive Skin Acne Cream Cleanser
NDC: 10742-1004 | Form: CREAM
Manufacturer: The Mentholatum Company
Category: otc | Type: HUMAN OTC DRUG LABEL
Date: 20241205

ACTIVE INGREDIENTS: BENZOYL PEROXIDE 50 mg/1 mL
INACTIVE INGREDIENTS: SODIUM LAUROYL SARCOSINATE; DISODIUM LAURETH SULFOSUCCINATE; XANTHAN GUM; RHODOMYRTUS TOMENTOSA FRUIT; SODIUM HYDROXIDE; GLYCERIN; SODIUM C14-16 OLEFIN SULFONATE; BUTYLENE GLYCOL; WATER; CITRIC ACID; CHLORPHENESIN; HYDROLYZED SOY PROTEIN (ENZYMATIC; 2000 MW); PEG-8 DIMETHICONE; PROPANEDIOL; CETOSTEARYL ALCOHOL; CAPRYL/CAPRAMIDOPROPYL BETAINE; PHENOXYETHANOL; SODIUM CITRATE; PORTULACA OLERACEA LEAF

Drug Facts - Oxy Sensitive Skin Acne Cream Cleanser

Active ingredient

Benzoyl peroxide 5%

Purpose

Benzoyl peroxide – Acne treatment

Uses

- for the treatment of acne
- clears acne pimples and allows skin to heal
- penetrates pores to control blackheads and whiteheads
- helps prevent new acne pimples from forming

Warnings

For external use only

Do not use if you

- have very sensitive skin
- are sensitive to benzoyl peroxide

When using this product

- skin irritation and dryness is more likely to occur if you use another topical acne medication at the same time. If irritation occurs, only use one topical acne medication at a time.
- avoid unnecessary sun exposure and use a sunscreen
- avoid contact with the eyes, lips, and mouth
- avoid contact with hair and dyed fabrics, which may be bleached by this product
- skin irritation may occur, characterized by redness, burning, itching, peeling, or possibly swelling. Irritation may be reduced by using the product less frequently or in a lower concentration.

Stop use and ask a doctor if

irritation becomes severe

If pregnant or breast-feeding,

ask a health professional before use.

Keep out of reach of children

If swallowed, get medical help or contact a Poison Control Center right away.

Directions

- wet face
- apply to hands then massage gently into face. If desired, leave on for 1-2 minutes.
- rinse thoroughly and pat dry
- follow with a non-comedogenic moisturizer if needed
- because excessive drying of the skin may occur, start with 1 application daily, then gradually increase to 2 or 3 times daily if needed or as directed by a doctor
- if bothersome dryness or peeling occurs, reduce application to once a day or every other day
- if going outside, apply sunscreen after using this product. If irritation or sensitivity develops, stop use of both products and ask a doctor.

Other information

- THIS PRODUCT MAY BLEACH HAIR OR DYED FABRICS
- KEEP TIGHTLY CLOSED
- avoid storing at temperatures above 100°F (38°C)

Inactive ingredients

water, cetostearyl alcohol, sodium C14-16 olefin sulfonate, disodium laureth sulfosuccinate, capryl/capramidopropyl betaine, xanthan gum, butylene glycol, chlorphenesin, citric acid, glycerin, hydrolyzed soy protein, PEG-8 dimethicone, phenoxyethanol, portulaca oleracea extract, propanediol, rhodomyrtus tomentosa fruit extract, sodium citrate, sodium hydroxide, sodium lauroyl sarcosinate

Questions?

1-877-636-2677 MON-FRI 9AM-5PM (EST)